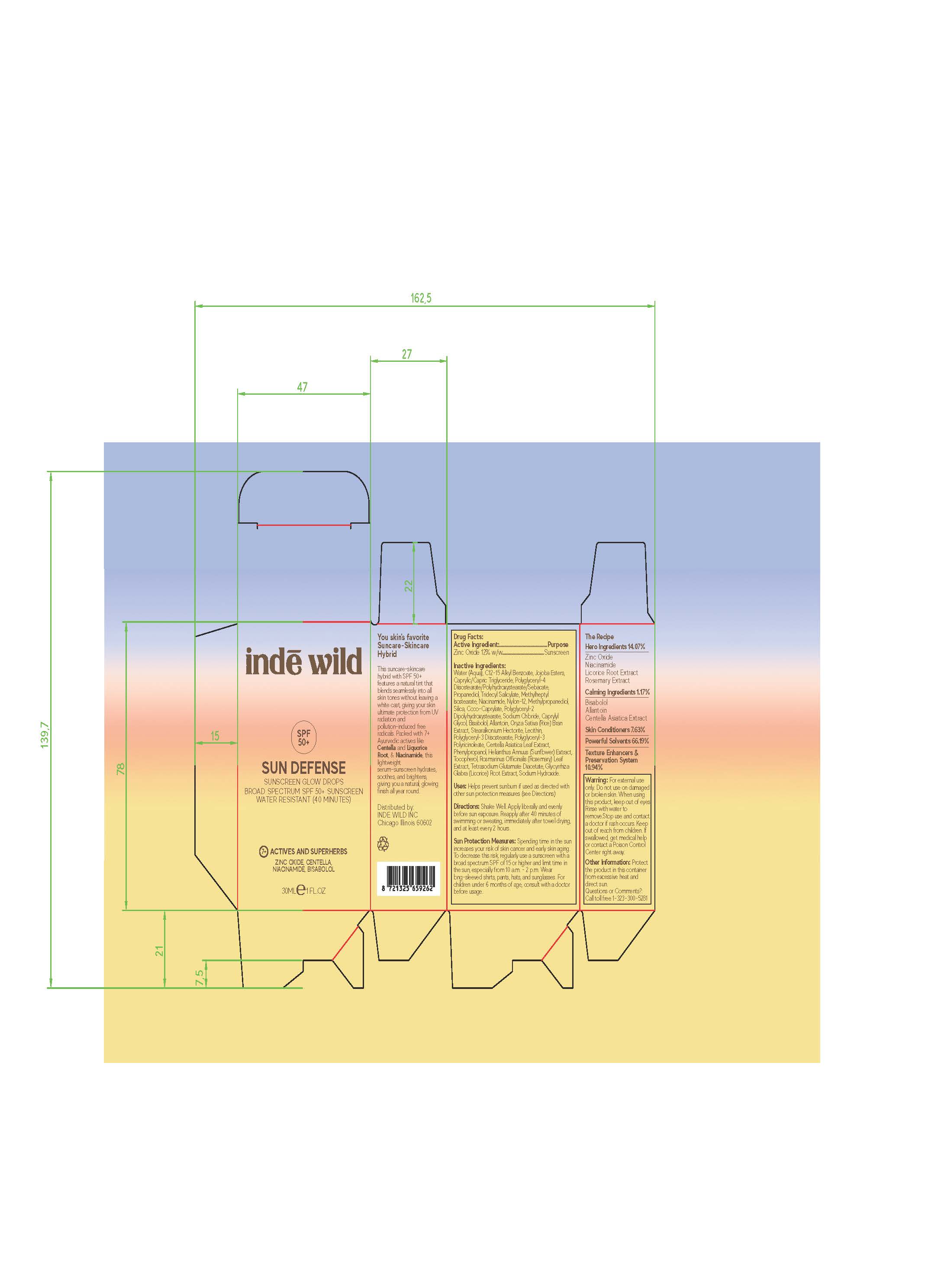 DRUG LABEL: inde wild SUN DEFENSE SPF 50 SUNSCREEN GLOW DROPS BROAD SPECTRUM
NDC: 83054-0001 | Form: LOTION
Manufacturer: INDE WILD PRIVATE LIMITED
Category: otc | Type: HUMAN OTC DRUG LABEL
Date: 20260108

ACTIVE INGREDIENTS: ZINC OXIDE 12 g/100 g
INACTIVE INGREDIENTS: TOCOPHEROL; WATER; C12-15 ALKYL BENZOATE; HYDROLYZED JOJOBA ESTERS (ACID FORM); CAPRYLIC/CAPRIC TRIGLYCERIDE; POLYGLYCERYL-4 DIISOSTEARATE/POLYHYDROXYSTEARATE/SEBACATE; PROPANEDIOL; TRIDECYL SALICYLATE; METHYLHEPTYL ISOSTEARATE; NIACINAMIDE; NYLON-12; METHYLPROPANEDIOL; SILICON DIOXIDE; COCO-CAPRYLATE; SODIUM CHLORIDE; POLYGLYCERYL-2 DIPOLYHYDROXYSTEARATE; CAPRYLYL GLYCOL; POLYGLYCERYL-3 DIISOSTEARATE; PHENYLPROPANOL; ROSMARINUS OFFICINALIS (ROSEMARY) LEAF OIL; LECITHIN, SOYBEAN; GLYCYRRHIZA GLABRA (LICORICE) ROOT; BISABOLOL; STEARALKONIUM HECTORITE; ORYZA SATIVA (RICE) BRAN; ALLANTOIN; CENTELLA ASIATICA LEAF; HELIANTHUS ANNUUS SEED WAX; TETRASODIUM GLUTAMATE DIACETATE; SODIUM HYDROXIDE

inde wild SUN DEFENSE SPF 50+ SUNSCREEN GLOW DROPS BROAD SPECTRUM

Active Ingredients

Zinc Oxide 12%

Uses

• helps prevent sunburn • if used as directed with other
sun protection measures (see Directions), decreases the
risk of skin cancer and early skin aging caused by the sun

Warnings

For external use only
Do not use on damaged or broken skin.
When using this product keep out of eyes. Rinse with water to remove.
Stop use and ask a docor if rash occurs
Keep out of reach of children. If swalled, get medical help or contact a Poison Control Center right away.

Directions

• apply liberally 15 minutes before sun exposure
• reapply:
• after 80 minutes of swimming or sweating
• immediately after towel drying
• at least every 2 hours
• Sun Protection Measures. Spending time in the sun increases your risk
of skin cancer and early skin aging. To decrease this risk, regularly use
a sunscreen with a broad spectrum SPF of 15 or higher and other sun
protection measures including:
• limit time in the sun, especially from 10 a.m. – 2 p.m.
• wear long-sleeve shirts, pants, hats, and sunglasses
• children under 6 months: Ask a doctor

Inactive ingredients

Water (Aqua), C12-15 Alkyl Benzoate, Jojoba Esters,
Caprylic/Capric Triglyceride, Polyglyceryl-4
Diisostearate/Polyhydroxystearate/Sebacate,
Propanediol, Tridecyl Salicylate, Methylheptyl
Isostearate, Niacinamide, Nylon-12, Methylpropanediol,
Silica, Coco-Caprylate, Polyglyceryl-2
Dipolyhydroxystearate, Sodium Chloride, Caprylyl
Glycol, Bisabolol, Allantoin, Oryza Sativa (Rice) Bran
Extract, Stearalkonium Hectorite, Lecithin,
Polyglyceryl-3 Diisostearate, Polyglyceryl-3
Polyricinoleate, Centella Asiatica Leaf Extract,
Phenylpropanol, Helianthus Annuus (Sunflower) Extract,
Tocopherol, Rosmarinus Officinalis (Rosemary) Leaf
Extract, Tetrasodium Glutamate Diacetate, Glycyrrhiza
Glabra (Licorice) Root Extract, Sodium Hydroxide.

Other Information

• protect the product in this container from excessive
heat and direct sun

Questions or Comments?

Conctact us at www.kinfield.com

Purpose

Purpose: Sunscreen

Keep out of reach of children. If product is swallowed, get medical help or contact a Poison Control Center right away.